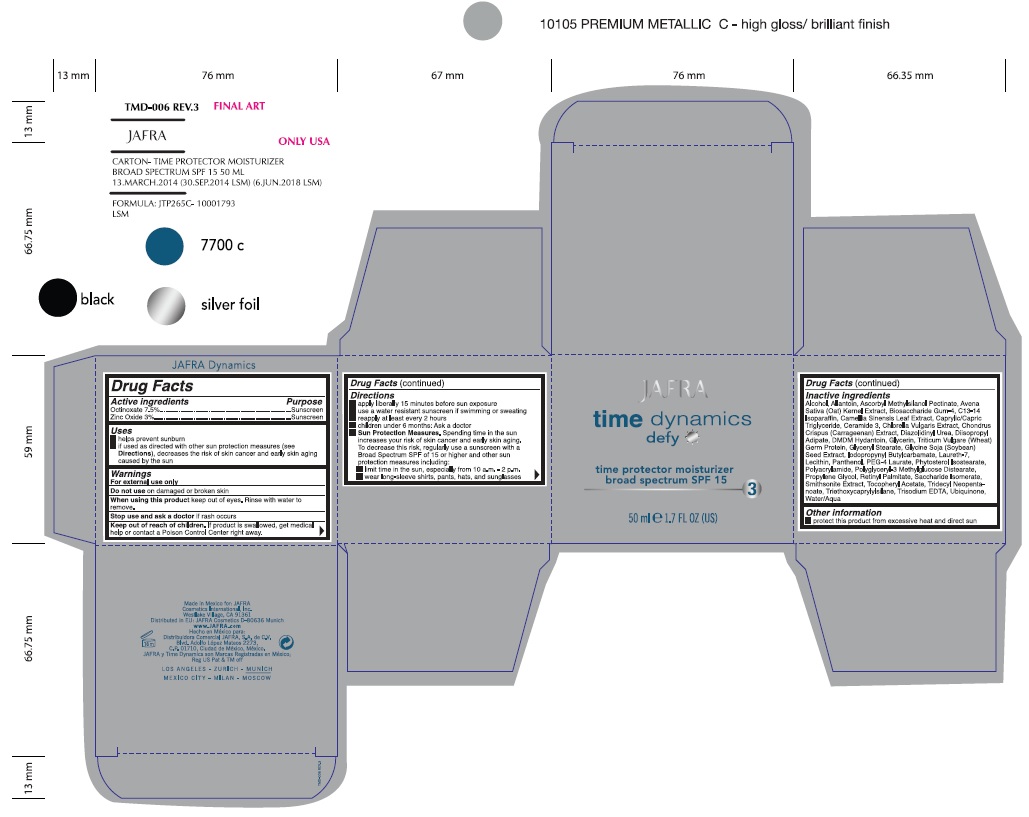 DRUG LABEL: Time Dynamics Defy Time Protector Moisturizer Broad Spectrum SPF 15
NDC: 68828-750 | Form: CREAM
Manufacturer: Jafra Cosmetics International
Category: otc | Type: HUMAN OTC DRUG LABEL
Date: 20230725

ACTIVE INGREDIENTS: OCTINOXATE 7.5 g/100 mL; ZINC OXIDE 3 g/100 mL
INACTIVE INGREDIENTS: ALCOHOL; ALLANTOIN; ASCORBYL METHYLSILANOL PECTINATE; OAT; BIOSACCHARIDE GUM-4; C13-14 ISOPARAFFIN; GREEN TEA LEAF; MEDIUM-CHAIN TRIGLYCERIDES; CERAMIDE NP; CHLORELLA VULGARIS; CHONDRUS CRISPUS CARRAGEENAN; DIAZOLIDINYL UREA; DIISOPROPYL ADIPATE; DMDM HYDANTOIN; GLYCERIN; WHEAT GERM; GLYCERYL MONOSTEARATE; SOYBEAN; IODOPROPYNYL BUTYLCARBAMATE; LAURETH-7; LECITHIN, SOYBEAN; PANTHENOL; PEG-4 LAURATE; POLYACRYLAMIDE (1500 MW); POLYGLYCERYL-3 METHYLGLUCOSE DISTEARATE; PROPYLENE GLYCOL; VITAMIN A PALMITATE; SACCHARIDE ISOMERATE; .ALPHA.-TOCOPHEROL ACETATE; TRIDECYL NEOPENTANOATE; TRIETHOXYCAPRYLYLSILANE; EDETATE TRISODIUM; UBIDECARENONE; WATER

Active Ingredients

Octinoxate 7.5%

Zinc Oxide 3%

Purpose

Sunscreen

Uses

Helps prevent sunburn
If used as directed with other sun protection measures (see Directions), decreases the risk of skin cancer and early skin aging caused by the sun.

Warnings

For external use only

Do not useon damaged or broken skin

When using this productkeep out of eyes. Rinse with water to remove.

Stop use and ask a doctorif rash occurs

Keep out of reach of children.If swallowed, get medical help or contact a Poison Control Center right away.

Directions

- apply liberally 15 minutes before sun exposure
- use a water resistant sunscreen if swimming or sweating
- reapply at least every 2 hours
- children under 6 months: Ask a doctor
- Sun Protection Measures.Spending time in the sun increases your risk of skin cancer and early skin aging. To decrease this risk, regularly use a sunscreen with a Broad Spectrum value of SPF 15 or higher and other sun protection measures including:
- limit time in the sun, especially from 10a.m - 2p.m.
- wear long-sleeve shirts, pants, hats, and sunglasses

Inactive Ingredients

Alcohol, Allantoin, Ascorbyl Methylsilanol Pectinate, Avena Sativa (Oat) Kernel Extract, Biosaccharide Gum-4, C13-14 Isoparaffin, Camellia Sinensis Leaf Extract, Caprylic/Capric Triglylceride, Ceramide 3, Chlorella Vulgaris Extract, Chondrus Crispus (Carrageenan) Extract, Diazolidinyl Urea, Diisopropyl Adipate, DMDM Hydantoin, Glycerin, Triticum Vulgare (Wheat) Germ Protein, Glyceryl Stearate, Glycine Soja (Soybean) Seed Extract, Iodopropynyl Bulylcarbamate, Laureth-7, Lecithin, Panthenol, PEG-4 Laurate, Phytosterol Isostearate, Polyacrylamide, Polyglyceryl-3 Methylglucose Distearate, Propylene Glycol, Retinyl Palmitate, Saccharide Isomerate, Smithsonite Extract, Tocopheryl Acetate, Tridecyl Neopentanoate, Triethoxycaprylylsilane, Trisodium EDTA, Ubiquinone, Water/Aqua

Other information

Protect this product from excessive heat and direct sun